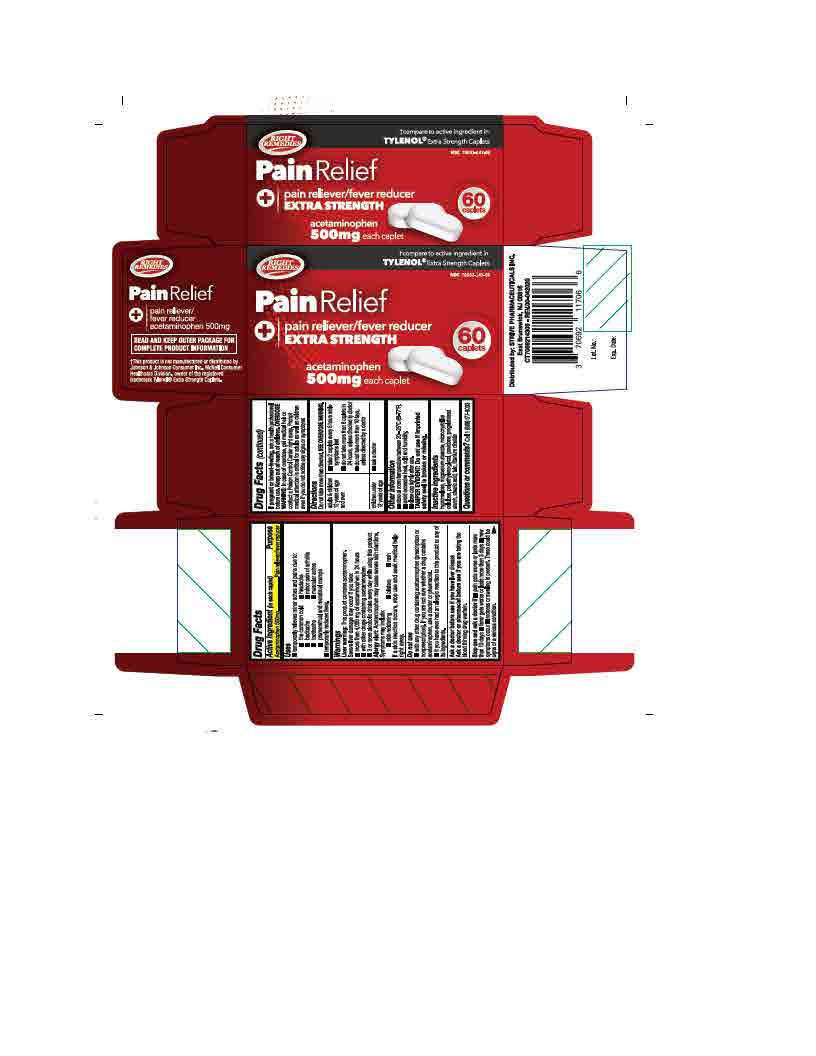 DRUG LABEL: Acetaminophen
NDC: 70692-399 | Form: TABLET
Manufacturer: Strive Pharmaceuticals Inc.
Category: otc | Type: HUMAN OTC DRUG LABEL
Date: 20220412

ACTIVE INGREDIENTS: ACETAMINOPHEN 500 mg/1 1
INACTIVE INGREDIENTS: TITANIUM DIOXIDE; POVIDONE; STEARIC ACID; CELLULOSE, MICROCRYSTALLINE; HYPROMELLOSES; MAGNESIUM STEARATE; TALC; STARCH, CORN; POLYETHYLENE GLYCOL 400

Acetaminophen 500mg

ACTIVE INGREDIENT

Acetaminophen 500mg

INACTIVE INGREDIENT

hypromellose, magnesium stearate, microcrystalline cellulose, polyethylene glycol, povidone, pregelatinized starch, stearic acid, talc, titanium dioxide

DOSAGE AND ADMINISTRATION

- do not take more than directed.SEE OVERDOSE WARNING

adults and children 12 years of age and over | - take 2 caplets every 6 hours while symptoms last - do not take more than 6 caplets in 24 hours, unless directed by a doctor - do not use for more than 10 days unless directed by a doctor
children under 12 years of age | ask a doctor

INDICATIONS AND USAGE

*temporarily relieves minor aches and pains due to:

- the common cold
- headache
- backache
- minor pain of arthritis
- toothache
- muscular aches
- premenstrual and menstrual cramps

*temporarily reduces fever

WARNINGS

Liver warning:

This product contains acetaminophen. Severe liver damage may occur if you take:

- more than 4000mg of acetaminophen in 24 hours
- with other drugs containing acetaminophen
- 3 or more alcoholic drinks every day while using this product

Allergy alert:

Acetaminophen may cause severe skin reactions. Symptoms may include:

- skin reddening
- blisters
- rash

if a skin reaction occurs, stop use and seek medical help right away

Do not use

- with any other drug containing acetaminophen (prescription or non prescription). If you are not sure whether a drug contains acetaminophen, ask a doctor or pharmacist.
- if you are allergic to acetaminophen or any of the inactive ingredients in this product

Ask a doctor before use if you have

- liver disease

Ask a doctor or a pharmacist before use if

you are taking the blood thinning drug warfarin

Stop use and ask a doctor if

- pain gets worse or lasts more than 10 days
- fever gets worse or lasts more than 3 days
- new symptoms occur
- redness or swelling is present

These could be signs of a serious comdition

If pregnant or breast-feeding,

ask a health professional before use

Keep out of reach of children

Overdose warning: In case of overdose, get medical help or contact a Poison Control Center right away. Prompt medical attention is critical for adults as well as children even if do not notice any signs or symptoms.

Keep out of reach of children

Overdose Warning: In case of accidental overdose, get medical help or contact a Poison Control Center right away. Prompt medical attention is critical for adults as well as for children even if you do not notice any signs or symptoms.

PURPOSE

Pain reliever / Fever reducer

OTHER SAFETY INFORMATION

- store at room temperature between 20ºC - 25ºC (68ºF - 77ºF)
- avoid excessive heat, cold and humidity
- close cap tightly after use